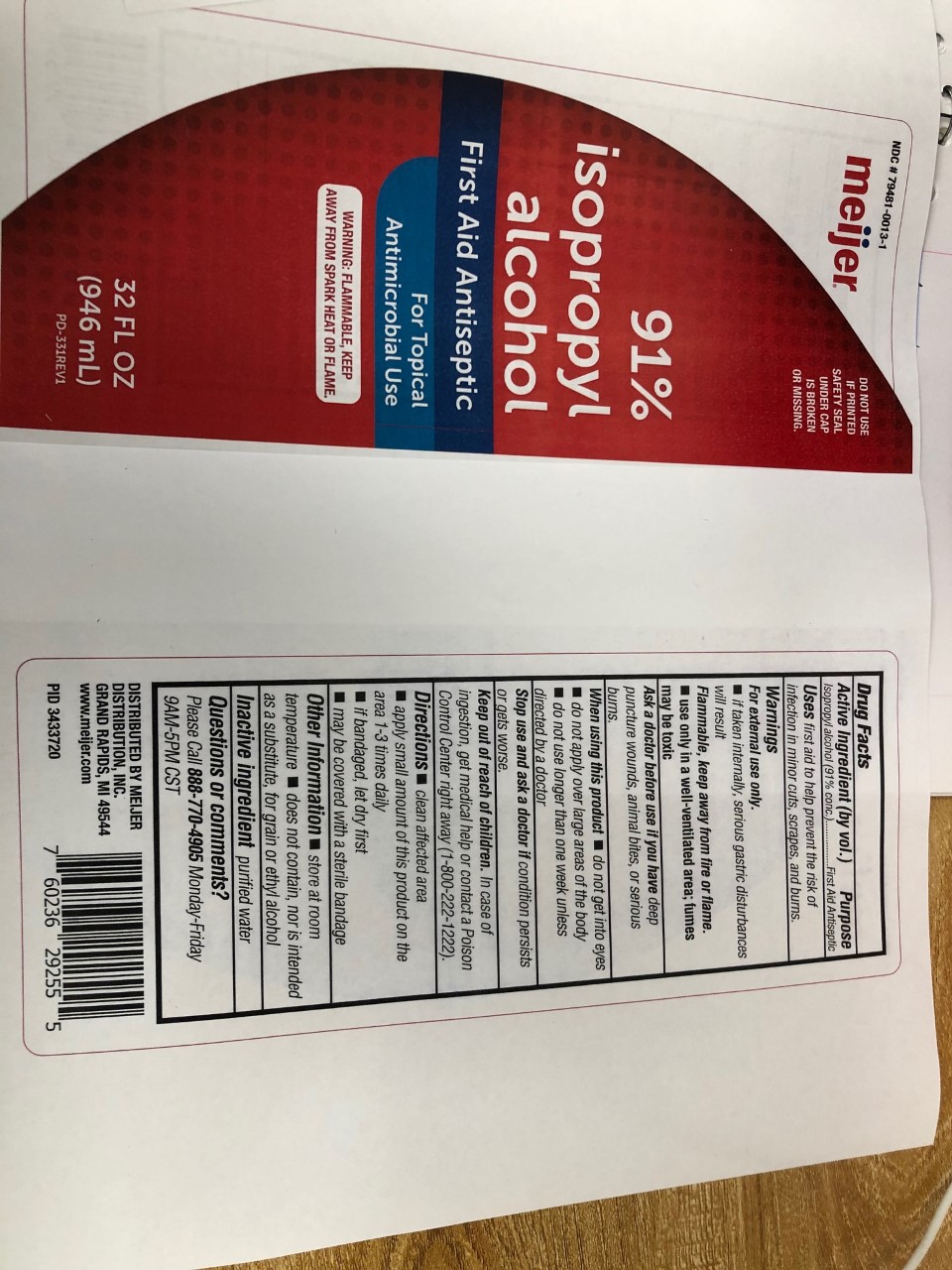 DRUG LABEL: 91% Isopropyl Alcohol
NDC: 79481-0013 | Form: LIQUID
Manufacturer: Meijer
Category: otc | Type: HUMAN OTC DRUG LABEL
Date: 20210311

ACTIVE INGREDIENTS: ISOPROPYL ALCOHOL 91 mL/100 mL
INACTIVE INGREDIENTS: WATER

Meijer 91% IPA

Meijer 91% IPA

This is a first aid antiseptic. It is manufactured using only the following United States Pharmacopoeia (USP) grade ingredients:

1. Isopropyl Alcohol (91%, v/v) in an aqueous solution
2. Sterile distilled water or boiled cold water.

The firm does not add other active or inactive ingredients.

Active Ingredient(s)

Isopropyl Alcohol 91% v/v. Purpose: Antiseptic

Purpose

Antiseptic

Use

First aid to help prevent the risk of infection in minor cuts, scrapes, and burns.

Warnings

For external use only. If taken internally, serious gastric disturbances will result. Flammable. Keep away from heat or flame. Use only in well-ventilated area; fumes may be toxic.

When using this product

- do not get into eyes
- do not apply over large areas of the body
- do not use longer than on week unless directed by a doctor

When using this product do not get into eyes

do not apply over large areas of the body

do not use longer than one week unless directed by a doctor

Stop use and ask a doctor if condition persists or gets worse.

Keep out of reach of children. In case of ingestion, get medical help or contact a Poison Control Center right away (1-800-222-1222)

Other information

- Store at room temperature
- does not contain, nor is intended as a substitute, for grain or ethyl alcohol

Inactive ingredients

purified water